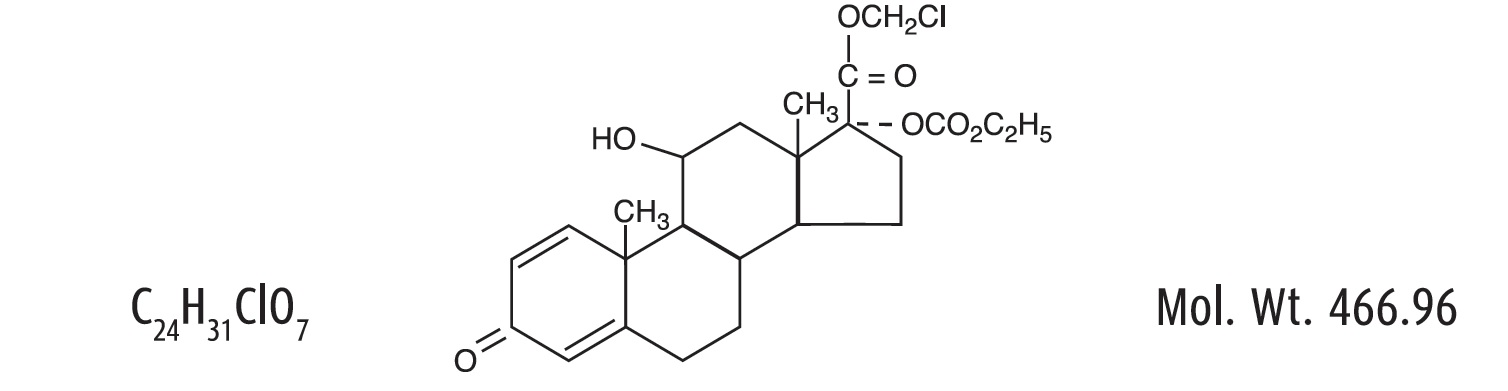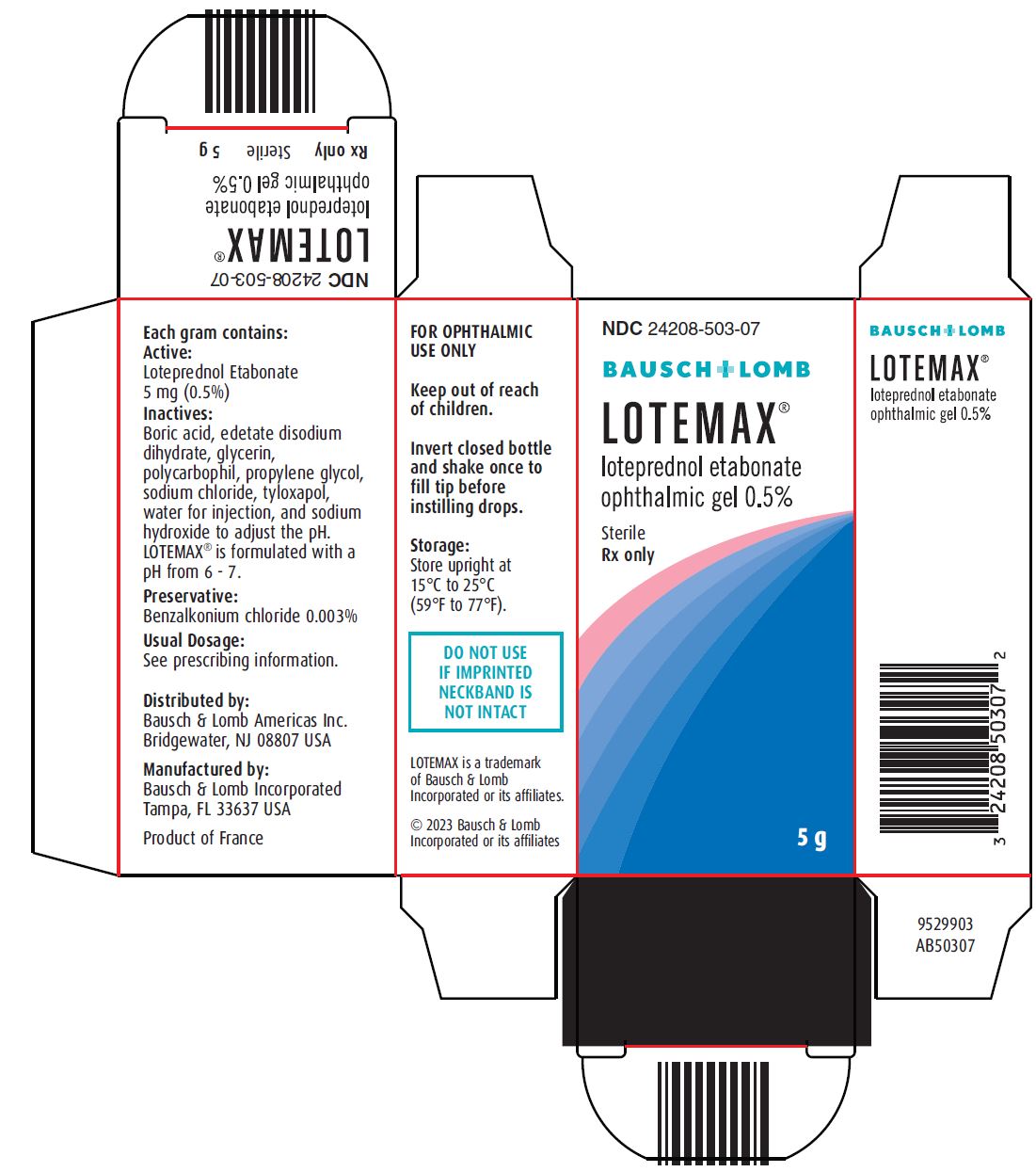 DRUG LABEL: LOTEMAX
NDC: 24208-503 | Form: GEL
Manufacturer: Bausch & Lomb Incorporated
Category: prescription | Type: HUMAN PRESCRIPTION DRUG LABEL
Date: 20241024

ACTIVE INGREDIENTS: LOTEPREDNOL ETABONATE 5 mg/1 g
INACTIVE INGREDIENTS: BORIC ACID; EDETATE DISODIUM; GLYCERIN; POLYCARBOPHIL; PROPYLENE GLYCOL; SODIUM CHLORIDE; TYLOXAPOL; WATER; SODIUM HYDROXIDE; BENZALKONIUM CHLORIDE

HIGHLIGHTS OF PRESCRIBING INFORMATION

These highlights do not include all the information needed to use LOTEMAXsafely and effectively. See full prescribing information for LOTEMAX.
LOTEMAX®(loteprednol etabonate ophthalmic gel), for topical ophthalmic use
Initial U.S. Approval: 1998

1 INDICATIONS AND USAGE

LOTEMAX is a corticosteroid indicated for the treatment of postoperative inflammation and pain following ocular surgery. (1)

2 DOSAGE AND ADMINISTRATION

- Invert closed bottle and shake once to fill tip before instilling drops. (2)
- Apply one to two drops of LOTEMAX into the conjunctival sac of the affected eye four times daily beginning the day after surgery and continuing throughout the first 2 weeks of the postoperative period. (2)

3 DOSAGE FORMS AND STRENGTHS

LOTEMAX is a sterile preserved ophthalmic gel containing 5 mg of loteprednol etabonate per gram of gel. (3)

4 CONTRAINDICATIONS

LOTEMAX is contraindicated in most viral diseases of the cornea and conjunctiva including epithelial herpes simplex keratitis (dendritic keratitis), vaccinia, and varicella, in mycobacterial infection of the eye and fungal diseases of ocular structures. (4)

5 WARNINGS AND PRECAUTIONS

- Intraocular pressure (IOP) increase - Prolonged use of corticosteroids may result in glaucoma with damage to the optic nerve, defects in visual acuity and fields of vision. If this product is used for 10 days or longer, IOP should be monitored. (5.1)
- Cataracts - Use of corticosteroids may result in posterior subcapsular cataract formation. (5.2)
- Delayed healing – The use of steroids after cataract surgery may delay healing and increase the incidence of bleb formation. In those diseases causing thinning of the cornea or sclera, perforations have been known to occur with the use of topical steroids. The initial prescription and renewal of the medication order should be made by a physician only after examination of the patient with the aid of magnification such as slit lamp biomicroscopy and, where appropriate, fluorescein staining. (5.3)
- Bacterial infections – Prolonged use of corticosteroids may suppress the host response and thus increase the hazard of secondary ocular infections. In acute purulent conditions, steroids may mask infection or enhance existing infection. (5.4)
- Viral infections – Employment of a corticosteroid medication in the treatment of patients with a history of herpes simplex requires great caution. Use of ocular steroids may prolong the course and may exacerbate the severity of many viral infections of the eye (including herpes simplex). (5.5)
- Fungal infections – Fungal infections of the cornea are particularly prone to develop coincidentally with long-term local steroid application. Fungus invasion must be considered in any persistent corneal ulceration where a steroid has been used or is in use. (5.6)

6 ADVERSE REACTIONS

The most common adverse drug reactions (2-5%) were anterior chamber inflammation, eye pain, and foreign body sensation. (6)

To report SUSPECTED ADVERSE REACTIONS, contact Bausch & Lomb Incorporated at 1-800-553-5340 or FDA at 1-800-FDA-1088 or www.fda.gov/medwatch.

FULL PRESCRIBING INFORMATION

1 INDICATIONS AND USAGE

LOTEMAX®(loteprednol etabonate ophthalmic gel) 0.5% is a corticosteroid indicated for the treatment of post-operative inflammation and pain following ocular surgery.

2 DOSAGE AND ADMINISTRATION

Invert closed bottle and shake once to fill tip before instilling drops.

Apply one to two drops of LOTEMAX into the conjunctival sac of the affected eye four times daily beginning the day after surgery and continuing throughout the first 2 weeks of the post-operative period.

3 DOSAGE FORMS AND STRENGTHS

LOTEMAX (loteprednol etabonate ophthalmic gel) is a sterile preserved ophthalmic gel containing 5 mg of loteprednol etabonate per gram of gel.

4 CONTRAINDICATIONS

LOTEMAX is contraindicated in most viral diseases of the cornea and conjunctiva including epithelial herpes simplex keratitis (dendritic keratitis), vaccinia, and varicella, in mycobacterial infection of the eye and fungal diseases of ocular structures.

5 WARNINGS AND PRECAUTIONS

5.1 Intraocular Pressure (IOP) Increase

Prolonged use of corticosteroids, including LOTEMAX, may result in glaucoma with damage to the optic nerve, defects in visual acuity and fields of vision. Steroids should be used with caution in the presence of glaucoma. If this product is used for 10 days or longer, intraocular pressure should be monitored.

5.2 Cataracts

Use of corticosteroids may result in posterior subcapsular cataract formation.

5.3 Delayed Healing

The use of steroids after cataract surgery may delay healing and increase the incidence of bleb formation. In those diseases causing thinning of the cornea or sclera, perforations have been known to occur with the use of topical steroids. The initial prescription and renewal of the medication order should be made by a physician only after examination of the patient with the aid of magnification such as slit lamp biomicroscopy and, where appropriate, fluorescein staining.

5.4 Bacterial Infections

Prolonged use of corticosteroids may suppress the host response and thus increase the hazard of secondary ocular infections. In acute purulent conditions of the eye, steroids may mask infection or enhance existing infection.

5.5 Viral Infections

Employment of a corticosteroid medication in the treatment of patients with a history of herpes simplex requires great caution. Use of ocular steroids may prolong the course and may exacerbate the severity of many viral infections of the eye (including herpes simplex).

5.6 Fungal Infections

Fungal infections of the cornea are particularly prone to develop coincidentally with long-term local steroid application. Fungus invasion must be considered in any persistent corneal ulceration where a steroid has been used or is in use. Fungal cultures should be taken when appropriate.

5.7 Contact Lens Wear

Patients should not wear contact lenses during their course of therapy with LOTEMAX.

6 ADVERSE REACTIONS

Adverse reactions associated with ophthalmic steroids include elevated intraocular pressure, which may be associated with infrequent optic nerve damage, visual acuity and field defects, posterior subcapsular cataract formation, delayed wound healing and secondary ocular infection from pathogens including herpes simplex, and perforation of the globe where there is thinning of the cornea or sclera.

The most common adverse drug reactions reported in the clinical trials (2-5%) were anterior chamber inflammation, eye pain, and foreign body sensation.

8 USE IN SPECIFIC POPULATIONS

8.1 Pregnancy

Risk Summary

There are no adequate and well-controlled studies with loteprednol etabonate in pregnant women.

Loteprednol etabonate produced teratogenicity at clinically relevant doses in the rabbit and rat when administered orally during pregnancy. Loteprednol etabonate produced malformations when administered orally to pregnant rabbits at doses ≥1.2 times the recommended human ophthalmic dose (RHOD) and to pregnant rats at doses ≥ 30 times the RHOD. In pregnant rats receiving oral doses of loteprednol etabonate during the period equivalent to the last trimester of pregnancy through lactation in humans, survival of offspring was reduced at doses ≥3 times the RHOD. Maternal toxicity was observed in rats at doses ≥ 304 times the RHOD, and a maternal no observed adverse effect level (NOAEL) was established at 30 times the RHOD.

The background risk of major birth defects and miscarriage for the indicated population is unknown. However, the background risk in the U.S. general population of major birth defects is 2 to 4%, and of miscarriage is 15 to 20%, of clinically recognized pregnancies.

Data
Animal Data
Embryofetal studies were conducted in pregnant rabbits administered loteprednol etabonate by oral gavage on gestation days 6 to 18, to target the period of organogenesis. Loteprednol etabonate produced fetal malformations at doses ≥ 0.1 mg/kg (1.2 times the recommended human ophthalmic dose (RHOD) based on body surface area, assuming 100% absorption). Spina bifida (including meningocele) was observed at doses ≥ 0.1 mg/kg, and exencephaly and craniofacial malformations were observed at doses ≥ 0.4 mg/kg (4.9 times the RHOD). At 3 mg/kg (36 times the RHOD), loteprednol etabonate was associated with increased incidences of abnormal left common carotid artery, limb flexures, umbilical hernia, scoliosis, and delayed ossification. Abortion and embryofetal lethality (resorption) occurred at doses ≥ 6 mg/kg (73 times the RHOD). A NOAEL for developmental toxicity was not established in this study. The NOAEL for maternal toxicity in rabbits was 3 mg/kg/day.

Embryofetal studies were conducted in pregnant rats administered loteprednol etabonate by oral gavage on gestation days 6 to 15, to target the period of organogenesis. Loteprednol etabonate produced fetal malformations, including absent innominate artery at doses ≥ 5 mg/kg (30 times the RHOD); and cleft palate, agnathia, cardiovascular defects, umbilical hernia, decreased fetal body weight and decreased skeletal ossification at doses ≥ 50 mg/kg (304 times the RHOD). Embryofetal lethality (resorption) was observed at 100 mg/kg (608 times the RHOD). The NOAEL for developmental toxicity in rats was 0.5 mg/kg (3 times the RHOD). Loteprednol etabonate was maternally toxic (reduced body weight gain) at doses of ≥ 50 mg/kg/day. The NOAEL for maternal toxicity was 5 mg/kg.

A peri-/postnatal study was conducted in rats administered loteprednol etabonate by oral gavage from gestation day 15 (start of fetal period) to postnatal day 21 (the end of lactation period). At doses ≥ 0.5 mg/kg (3 times the clinical dose), reduced survival was observed in live-born offspring. Doses ≥ 5 mg/kg (30 times the RHOD) caused umbilical hernia/incomplete gastrointestinal tract. Doses ≥ 50 mg/kg (304 times the RHOD) produced maternal toxicity (reduced body weight gain, death), decreased number of live-born offspring, decreased birth weight, and delays in postnatal development. A developmental NOAEL was not established in this study. The NOAEL for maternal toxicity was 5 mg/kg.

8.2 Lactation

There are no data on the presence of loteprednol etabonate in human milk, the effects on the breastfed infant, or the effects on milk production. The developmental and health benefits of breastfeeding should be considered, along with the mother’s clinical need for LOTEMAX and any potential adverse effects on the breastfed infant from LOTEMAX.

8.4 Pediatric Use

The safety and effectiveness of LOTEMAX have been established in the pediatric population. Use of LOTEMAX in this population is supported by evidence from adequate and well-controlled trials of LOTEMAX in adults with additional data from a safety and efficacy trial in pediatric patients from birth to 11 years of age [see Clinical Studies (14)] .

8.5 Geriatric Use

No overall differences in safety and effectiveness have been observed between elderly and younger patients.

11 DESCRIPTION

Loteprednol etabonate is a corticosteroid. Its chemical name is chloromethyl 17α-[(ethoxycarbonyl)oxy]-11β-hydroxy-3-oxoandrosta-1,4-diene-17β-carboxylate. Its molecular formula is C24H31ClO7and its chemical structure is:

LOTEMAX®(loteprednol etabonate ophthalmic gel) 0.5% contains a sterile, topical corticosteroid for ophthalmic use. Loteprednol etabonate is a white to off-white powder.

Each gram contains:

- Active: loteprednol etabonate 5 mg (0.5%)
- Inactives: boric acid, edetate disodium dihydrate, glycerin, polycarbophil, propylene glycol, sodium chloride, tyloxapol, water for injection, and sodium hydroxide to adjust to a pH of between 6 and 7
- Preservative: benzalkonium chloride 0.003%

12 CLINICAL PHARMACOLOGY

12.1 Mechanism of Action

Corticosteroids inhibit the inflammatory response to a variety of inciting agents and probably delay or slow healing. They inhibit the edema, fibrin deposition, capillary dilation, leukocyte migration, capillary proliferation, fibroblast proliferation, deposition of collagen, and scar formation associated with inflammation. While glucocorticoids are known to bind to and activate the glucocorticoid receptor, the molecular mechanisms involved in glucocorticoid/glucocorticoid receptor-dependent modulation of inflammation are not clearly established. However, corticosteroids are thought to inhibit prostaglandin production through several independent mechanisms.

12.3 Pharmacokinetics

Loteprednol etabonate is lipid soluble and can penetrate into cells. Loteprednol etabonate is synthesized through structural modifications of prednisolone-related compounds so that it will undergo a predictable transformation to an inactive metabolite. Based upon in vivo and in vitro preclinical metabolism studies, loteprednol etabonate undergoes extensive metabolism to the inactive carboxylic acid metabolites, PJ-91 and PJ-90. The systemic exposure to loteprednol etabonate following ocular administration of LOTEMAX has not been studied in humans.

13 NONCLINICAL TOXICOLOGY

13.1 Carcinogenesis, Mutagenesis, Impairment of Fertility

Long-term animal studies have not been conducted to evaluate the carcinogenic potential of loteprednol etabonate. Loteprednol etabonate was not genotoxic in vitro in the Ames test, the mouse lymphoma tk assay, or in a chromosome aberration test in human lymphocytes, or in vivo in the single dose mouse micronucleus assay.

Treatment of female and male rats with doses ≥ 25 mg/kg/day of loteprednol etabonate (152 times the RHOD based on body surface area, assuming 100% absorption) prior to and during mating caused preimplantation loss and decreased the number of live fetuses/live births. The NOAEL for fertility in rats was 5 mg/kg/day (30 times the RHOD).

14 CLINICAL STUDIES

Adult Studies
In two randomized, multicenter, double-masked, parallel-group, vehicle-controlled studies in 813 subjects with post-operative inflammation, LOTEMAX was more effective compared to its vehicle in resolving anterior chamber inflammation and pain following cataract surgery. Primary endpoints were complete resolution of anterior chamber cells (cell count of 0) and no pain at post-operative day 8.

In these studies, LOTEMAX had a statistically significant higher incidence of subjects with complete clearing of anterior chamber cells (31% vs. 14-16%) and were pain-free at post-operative day 8 (73-76% vs. 42-46%).

Pediatric Study
The safety and effectiveness of LOTEMAX were evaluated in a pediatric study of patients from birth to less than 11 years of age (mean age of 3 years) undergoing cataract surgery. Patients were randomized to receive either LOTEMAX (54 patients) or prednisolone acetate ophthalmic suspension 1% (53 patients) four times daily for 14 days. At Day 14, the percentages of patients with complete clearing of anterior chamber inflammation were 57% in the LOTEMAX group and 63% in the prednisolone group.

16 HOW SUPPLIED/STORAGE AND HANDLING

LOTEMAX ®(loteprednol etabonate ophthalmic gel) 0.5% is a sterile ophthalmic gel supplied in a white low density polyethylene plastic bottle with a white controlled drop tip and a pink polypropylene cap in the following size:

1. NDC 24208-503-07 5 g in a 10 mL bottle

Storage:Store upright at 15ºC to 25ºC (59ºF to 77ºF).

17 PATIENT COUNSELING INFORMATION

Administration

Invert closed bottle and shake once to fill tip before instilling drops.

Risk of Contamination

Advise patients not to allow the dropper tip to touch any surface, as this may contaminate the gel.

Contact Lens Wear

Advise patients not to wear contact lenses when using LOTEMAX.

Risk of Secondary Infection

Advise the patient to consult a physician if pain develops, redness, itching or inflammation becomes aggravated.

Distributed by:
Bausch & Lomb Americas Inc.
Bridgewater, NJ 08807 USA

Manufactured by:
Bausch & Lomb Incorporated
Tampa, FL 33637 USA
LOTEMAX is a trademark of Bausch & Lomb Incorporated or its affiliates.

© 2023 Bausch & Lomb Incorporated or its affiliates

9269204 Folded

9269104 Flat

PACKAGE/LABEL PRINCIPAL DISPLAY PANEL

NDC24208-503-07

BAUSCH + LOMB
LOTEMAX®

loteprednol etabonate
ophthalmic gel 0.5%

Sterile
Rx only

5 g

9529903

AB50307